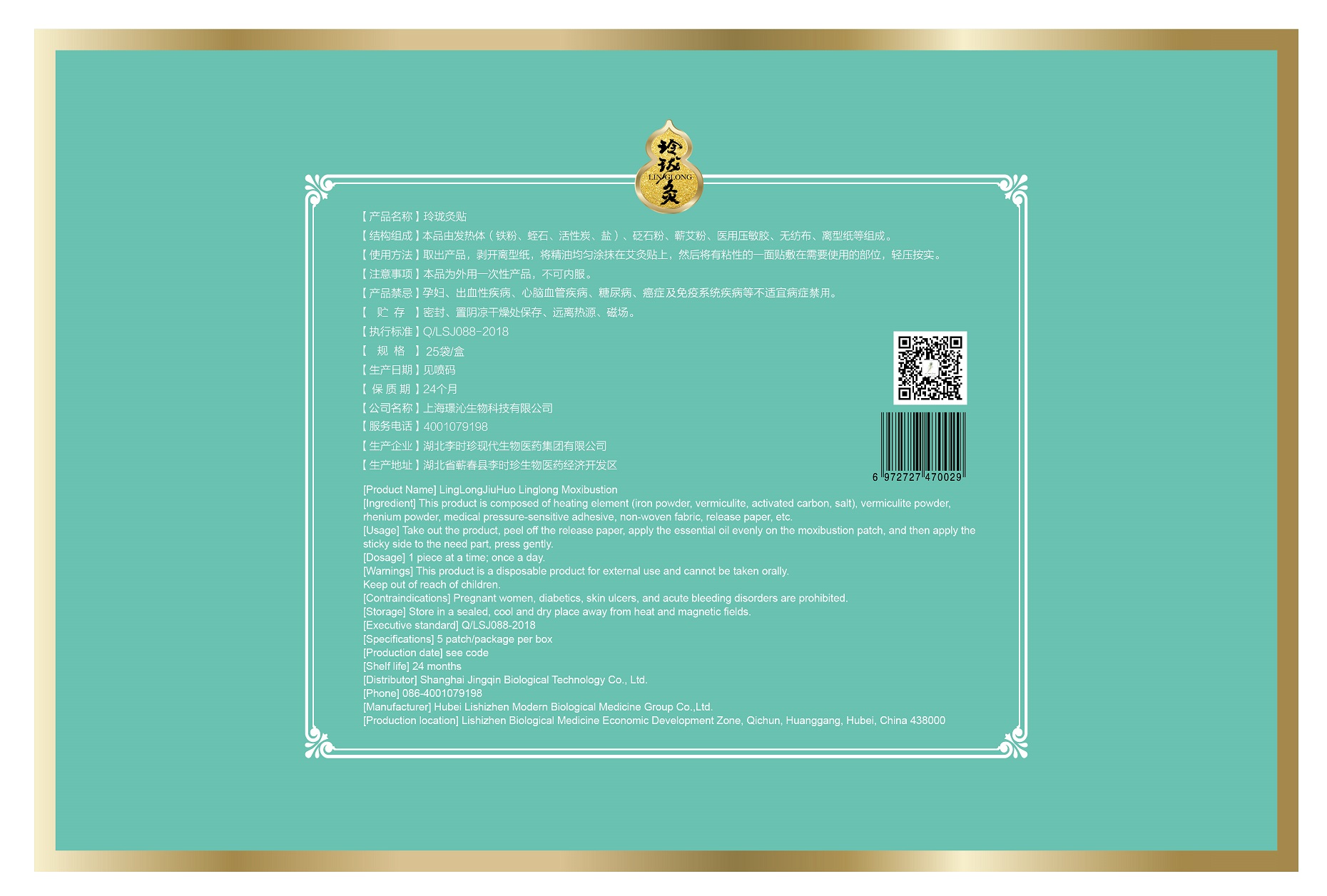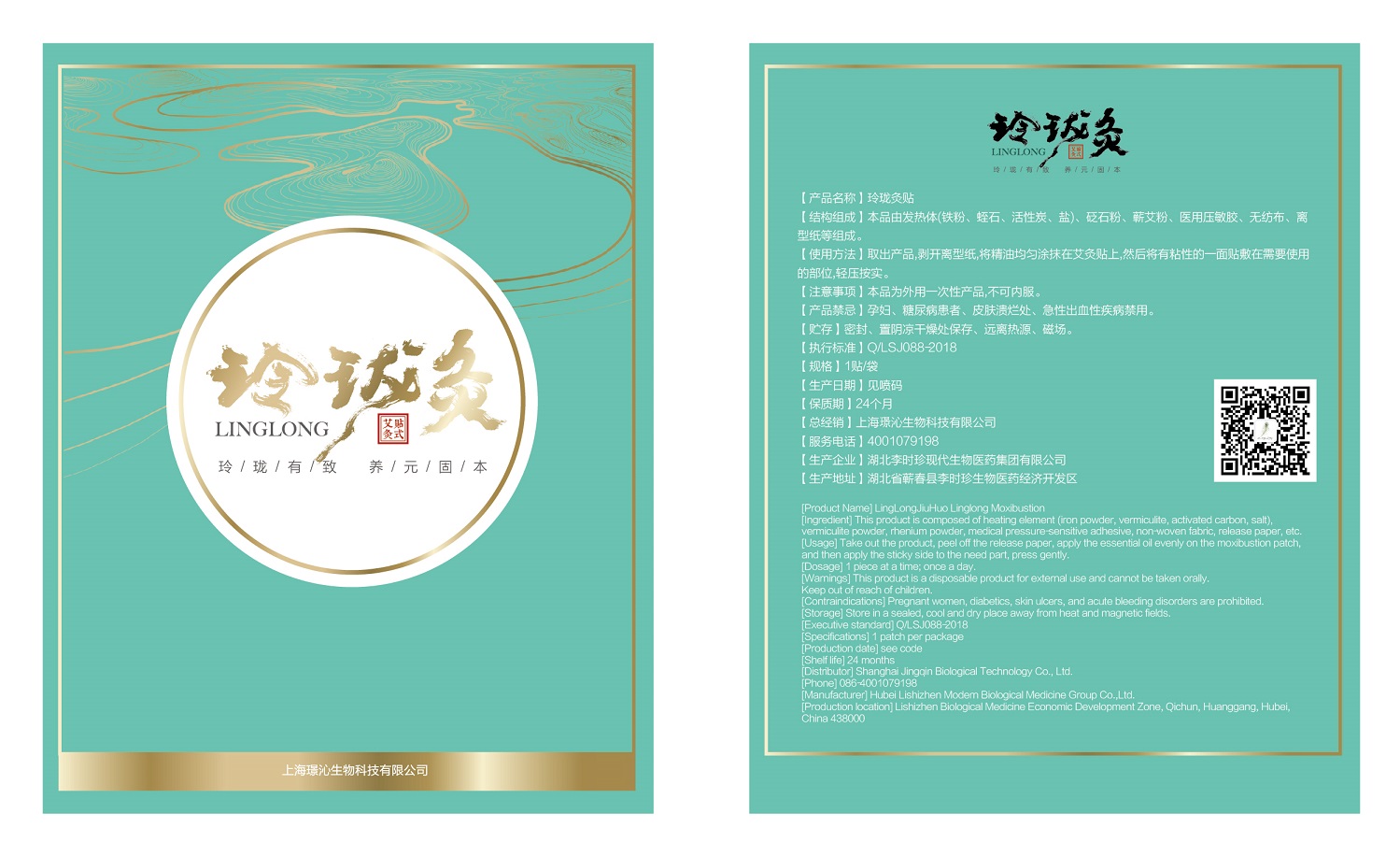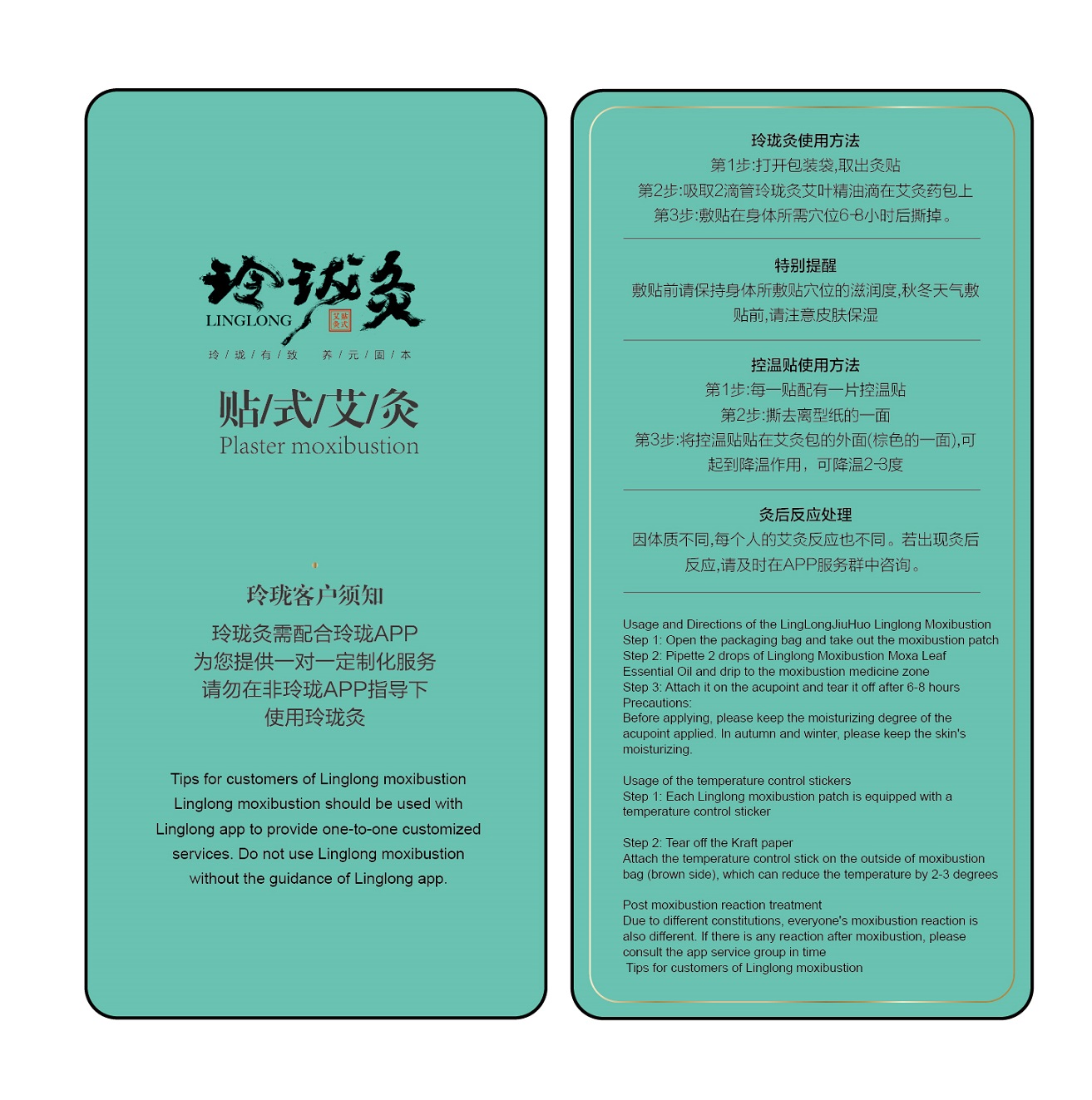 DRUG LABEL: LingLongJiuHuo Linglong Moxibustion
NDC: 73510-525 | Form: TAPE
Manufacturer: Shanghai Jingqin Biological Technology Co., Ltd.
Category: otc | Type: HUMAN OTC DRUG LABEL
Date: 20201026

ACTIVE INGREDIENTS: BUTYLENE GLYCOL 1.6 g/8 g
INACTIVE INGREDIENTS: HYDROXYETHYL CELLULOSE (280 MPA.S AT 2%) 0.128 g/8 g; WATER 6.2016 g/8 g; PHENOXYETHANOL 0.024 g/8 g; POLYETHYLENE GLYCOL 300000 0.04 g/8 g; CHLORPHENESIN 0.0064 g/8 g

LingLongJiuHuo Linglong Moxibustion, JingQin

Active ingredient

butylene glycol (20%)

Inactive ingredient

water (77.52%)

hydroxyethylcellulose (1.6%)

polyethylene glycol 300000 (0.5%)

phenoxyethanol (0.3%)

chlorphenesin (0.08%)

Purpose

It is a heat disposable paster incorporating chemicals that provides heat therapy for body.

When using

Conditioning neck, back, hands and feet and other rheumatism pain and spleen and stomach caused by cold injury, deficiency diarrhea and other conditions.

Do not use

If irritation or discomfort occurs, discontinue the use and consult a physician.

Stop use

If irritation or discomfort occurs, discontinue the use and consult a physician.

Ask doctor

If irritation or discomfort occurs, discontinue the use and consult a physician.

Ask doctor/pharmacist when you current use other drugs.

Keep out of reach of children and away from eyes and ears.

Questions

Please contact with us at the phone number on the package when you have any questions.

Pregnancy or breast feeding

Pregnant or breast feeding women shall follow doctor advice.

Indications & usage

Pain relief, hot release, warming uterus, hemostatic, can be used to improve the conditioning neck, back, hands and feet and other rheumatism pain and spleen and stomach caused by cold injury, deficiency diarrhea and other conditions.

Apply one paster on stomach venter.

Dosage & administration

1 piece at a time; once a day.

Dosage forms & strengths

It is a paster.

1 piece at a time; once a day.

The active ingredient strength is 20%.

Warnings

[Warnings] This product is a disposable product for external use and cannot be taken orally.

[Contraindications] Pregnant women, diabetics, skin ulcers, and acute bleeding disorders are prohibited.

If irritation or discomfort occurs, discontinue the use and consult a physician.

Very slippery on surfaces, clean spills immediately.

Keep out of reach of children and pets.